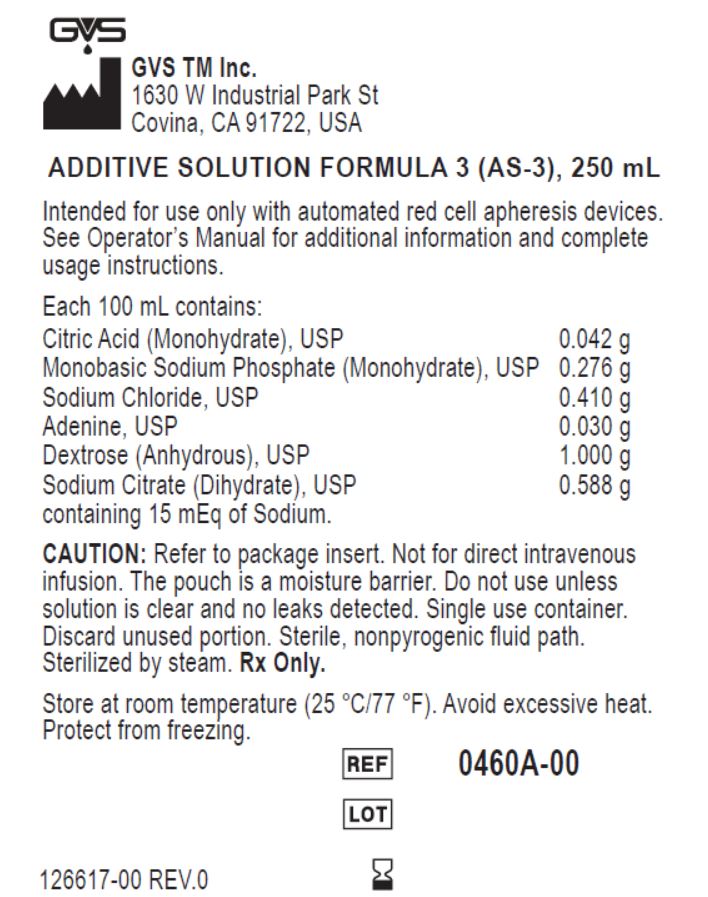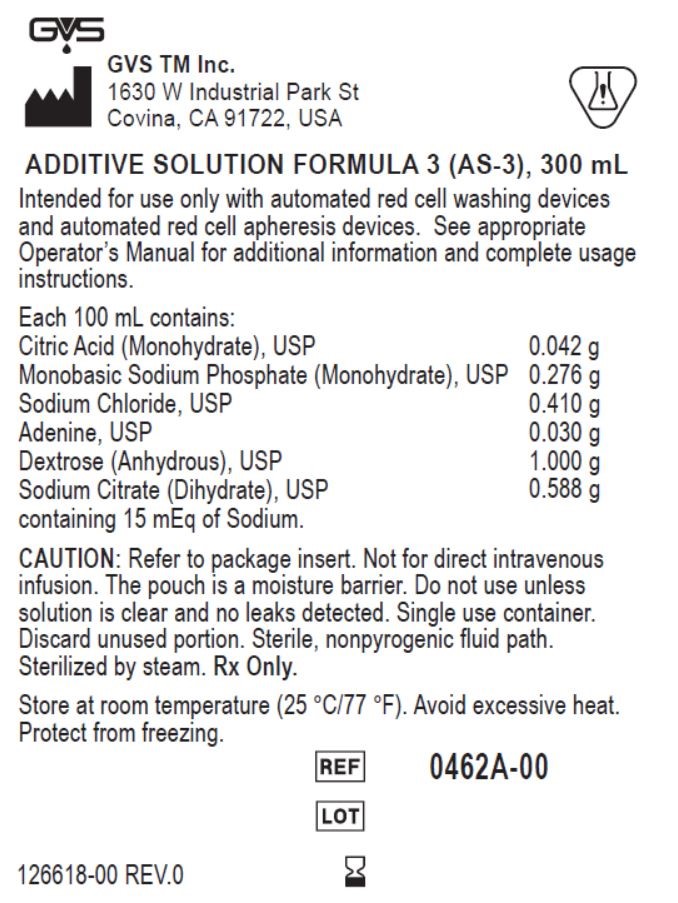 DRUG LABEL: AS-3
NDC: 87069-460 | Form: SOLUTION
Manufacturer: GVS TM INC
Category: prescription | Type: HUMAN PRESCRIPTION DRUG LABEL
Date: 20251106

ACTIVE INGREDIENTS: ADENINE 0.03 g/100 mL; DEXTROSE, UNSPECIFIED FORM 1 g/100 mL
INACTIVE INGREDIENTS: SODIUM CITRATE, UNSPECIFIED FORM; SODIUM CHLORIDE; CITRIC ACID MONOHYDRATE; SODIUM PHOSPHATE, MONOBASIC, MONOHYDRATE

AS 3 listing

Intended use of the device

Intended for use only with automated red cell washing devices
and automated red cell apheresis devices.

Storage and handling

Store at room temperature (25 °C/77 °F). Avoid excessive heat.
Protect from freezing

Warnings and precoutions section

See appropriate Operator’s Manual for additional information and complete usage instructions.

Not for direct intravenous infusion

Do not use unless solution is clear and no leaks detected

Single use container. Discard unused portion

Intended for use only with automated red cell washing and apheresis devices

Store at room temperature. Avoid excessive heat. Protect from freezing

DESCRIPTION

ADDITIVE SOLUTION FORMULA 3 (AS-3), 300 mL

Each 100 mL contains:
Citric Acid (Monohydrate), USP 0.042 g
Monobasic Sodium Phosphate (Monohydrate), USP 0.276 g
Sodium Chloride, USP 0.410 g
Adenine, USP 0.030 g
Dextrose (Anhydrous), USP 1.000 g
Sodium Citrate (Dihydrate), USP 0.588 g
containing 15 mEq of Sodium.
.

STATEMENT OF IDENTITY

ADDITIVE SOLUTION FORMULA 3 (AS-3), 300 ml

Warnings and precoutions

Not for direct intravenous infusion

Do not use unless solution is clear and no leaks detected

Single use container. Discard unused portion

Intended for use only with automated red cell washing and apheresis devices

See Operator’s Manual for additional information and complete usage instructions

Store at room temperature. Avoid excessive heat. Protect from freezing

INTENDED USE OF THE DEVICE

I Intended for use only with automated red cell apheresis devices.

Storage and handling

Store at room temperature (25 °C/77 °F). Avoid excessive heat.
Protect from freezing.

Description of the product

ADDITIVE SOLUTION FORMULA 3 (AS-3), 250 mL

Each 100 mL contains:
Citric Acid (Monohydrate), USP 0.042 g
Monobasic Sodium Phosphate (Monohydrate), USP 0.042 g
Sodium Chloride, USP 0.410 g
Adenine, USP 0.030 g
Dextrose (Anhydrous), USP 1.000 g
Sodium Citrate (Dihydrate), USP 0.588 g
containing 15 mEq of Sodium.

Statement of idenity

ADDITIVE SOLUTION FORMULA 3 (AS-3), 250 mL

Package label

Manufacturer: GVS TM Inc.
1630 W Industrial Park St
Covina, CA 91722, USA

ADDITIVE SOLUTION FORMULA 3 (AS-3), 300 mL
Intended for use only with automated red cell washing devices
and automated red cell apheresis devices. See appropriate
Operator’s Manual for additional information and complete usage
instructions.
Each 100 mL contains:
Citric Acid (Monohydrate), USP 0.042 g
Monobasic Sodium Phosphate (Monohydrate), USP 0.276 g
Sodium Chloride, USP 0.410 g
Adenine, USP 0.030 g
Dextrose (Anhydrous), USP 1.000 g
Sodium Citrate (Dihydrate), USP 0.588 g
containing 15 mEq of Sodium.
CAUTION: Refer to package insert. Not for direct intravenous
infusion. The pouch is a moisture barrier. Do not use unless
solution is clear and no leaks detected. Single use container.
Discard unused portion. Sterile, nonpyrogenic fluid path.
Sterilized by steam. Rx Only.
Store at room temperature (25 °C/77 °F). Avoid excessive heat.
Protect from freezing.

REF symbol: 0462A-00

LOT symbol

expiry date symbol

template revision number: 126618-00 REV.0

Package label

Manufacturer: GVS TM Inc.
1630 W Industrial Park St
Covina, CA 91722, USA

ADDITIVE SOLUTION FORMULA 3 (AS-3), 250 mL
Intended for use only with automated red cell apheresis devices. See appropriate
Operator’s Manual for additional information and complete usage
instructions.
Each 100 mL contains:
Citric Acid (Monohydrate), USP 0.042 g
Monobasic Sodium Phosphate (Monohydrate), USP 0.276 g
Sodium Chloride, USP 0.410 g
Adenine, USP 0.030 g
Dextrose (Anhydrous), USP 1.000 g
Sodium Citrate (Dihydrate), USP 0.588 g
containing 15 mEq of Sodium.
CAUTION: Refer to package insert. Not for direct intravenous
infusion. The pouch is a moisture barrier. Do not use unless
solution is clear and no leaks detected. Single use container.
Discard unused portion. Sterile, nonpyrogenic fluid path.
Sterilized by steam. Rx Only.
Store at room temperature (25 °C/77 °F). Avoid excessive heat.
Protect from freezing.

REF symbol: 0460A-00

LOT symbol

expiry date symbol

template revision number 126617-00 REV.0